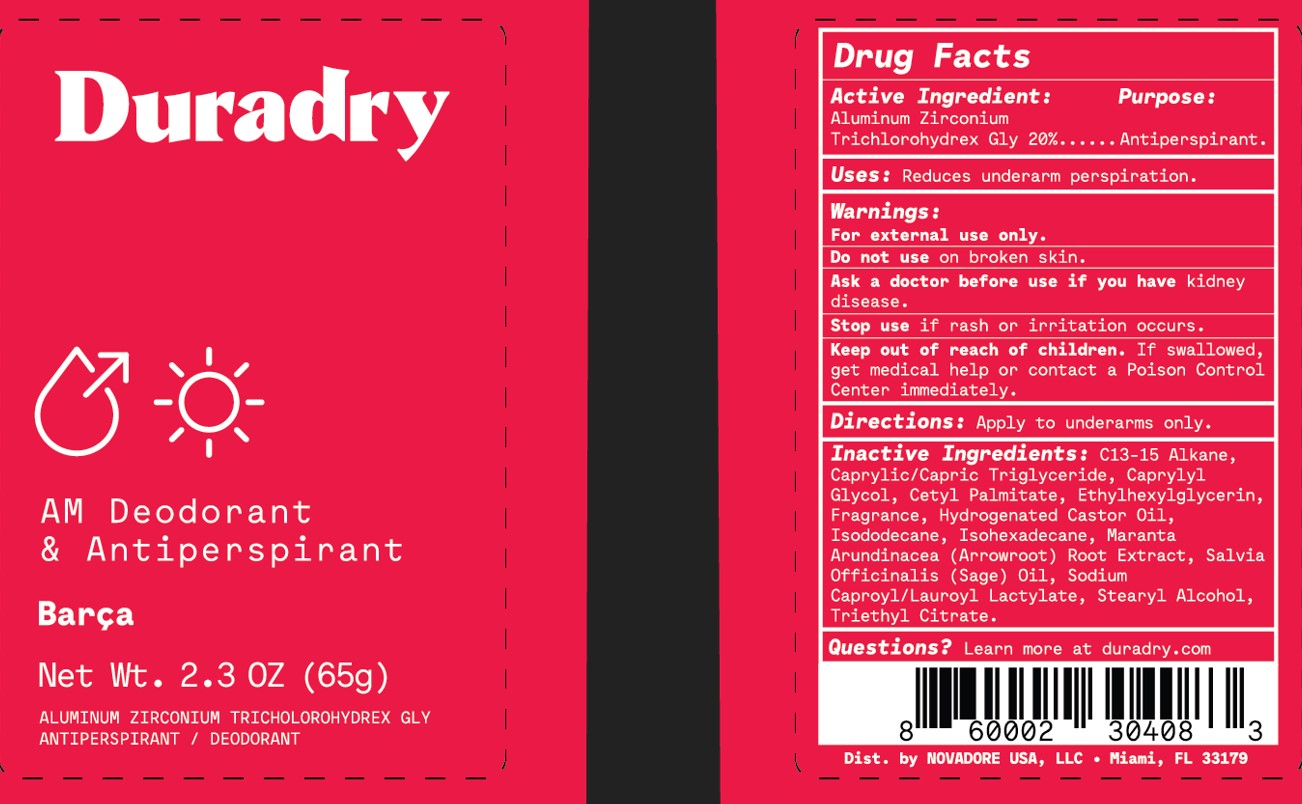 DRUG LABEL: Duradry
NDC: 58443-0430 | Form: STICK
Manufacturer: Prime Enterprises Inc.
Category: otc | Type: HUMAN OTC DRUG LABEL
Date: 20211028

ACTIVE INGREDIENTS: ALUMINUM ZIRCONIUM TRICHLOROHYDREX GLY 200 mg/1 g
INACTIVE INGREDIENTS: TRIETHYL CITRATE; ETHYLHEXYLGLYCERIN; FRAGRANCE CLEAN ORC0600327; MARANTA ARUNDINACEA ROOT; CAPRYLYL GLYCOL; CETYL PALMITATE; ISODODECANE; ISOHEXADECANE; C13-15 ALKANE; SAGE OIL; STEARYL ALCOHOL; MEDIUM-CHAIN TRIGLYCERIDES; HYDROGENATED CASTOR OIL

Duradry AM Deodorant & Antiperspirant Barca

Active Ingredient:

Aluminum Zirconium Trichlorohydrex Gly 20%

Purpose:

Antiperspirant.

Uses:

Reduces underarm perspiration.

Warnings:

For external use only.

Do not use on broken skin.

Ask a doctor before use if you have kidney disease.

Keep out of reach of children. If swallowed, get medical help or contact a Poison Control Center immediately.

Stop use if rash or irritation occurs.

Directions:

Apply to underarms only.

Inactive Ingredients:

C13-15 Alkane, Caprylic/Capric Triglyceride, Caprylyl Glycol, Cetyl Palmitate, Ethylhexylglycerin, Fragrance, Hydrogenated Castor Oil, Isododecane, Isohexadecane, Maranta Arundinacea (Arrowroot) Root Extract, Salvia Officinalis (Sage) Oil, Sodium Caproyl/Lauroyl Lactylate, Stearyl Alcohol, Triethyl Citrate

Questions?

Learn more at duradry.com